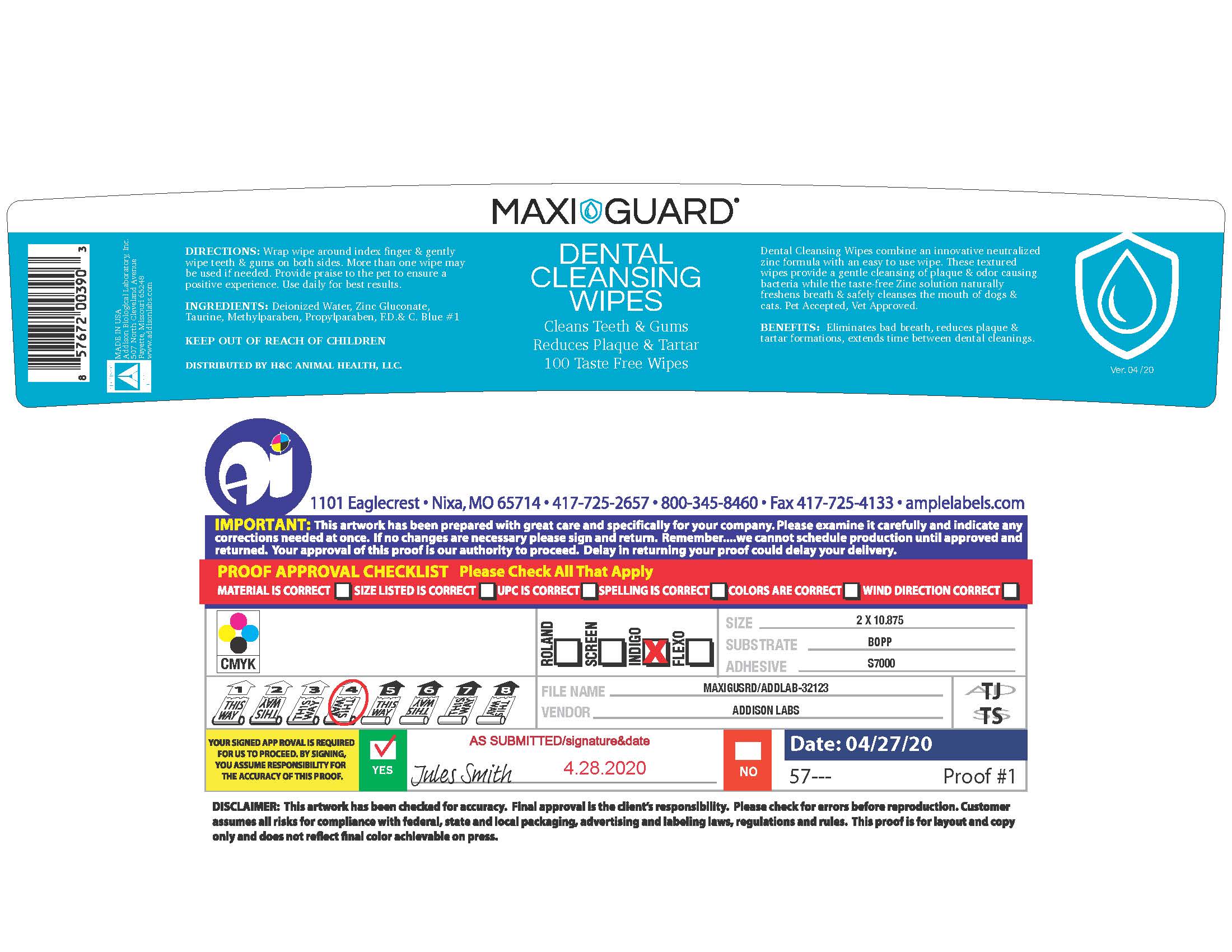 DRUG LABEL: Maxi/Guard Dental Cleansing Wipes
NDC: 86137-4509 | Form: SOLUTION
Manufacturer: H&C Animal Health
Category: animal | Type: OTC ANIMAL DRUG LABEL
Date: 20251201

ACTIVE INGREDIENTS: ZINC GLUCONATE .0165 1/1 1
INACTIVE INGREDIENTS: WATER; TAURINE; METHYLPARABEN; PROPYLPARABEN; FD&C BLUE NO. 1

Maxi/Guard Dental Cleansing Wipes

INFORMATION FOR OWNERS/CAREGIVERS

Dental Cleansing Wipes combine an innovative neutralized zinc formulation with an easy to use wipe. These textured wipes provide a gentle cleansing of plaque & odor causing bacteria while the taste-free Zinc solution naturally freshens the breath & safely cleanses the mouth of dogs & cats. Pet Accapted, Vet Approved.

BENEFITS: Eliminates bad breath, reduces plaque & tartar formations, extends time between dental cleanings.

INSTRUCTIONS FOR USE

DIRECTIONS: Wrap wipe around index finger & gently wipe teeth & gums on both sides. More than one wipe may be used if needed. Provide praise to the pet to ensure a positive experience. Use daily for best results.

Keep out of reach of children.

INACTIVE INGREDIENT

INGREDIENTS: Deionized Water, Zinc Gluconate, Taurine, Methylparaben, Propylparaben, F.D.& C. Blue #1.

DENTAL CLEANSING WIPES

Maxi/Guard®
Dental Cleansing Wipes

Cleans Teeth & Gums

Reduces Plaque & Tartar
100 Taste Free Wipes

Dental Cleansing Wipes combine an innovative neutralized zinc formulation with an easy to use wipe. These textured wipes provide a gentle cleansing of plaque & odor causing bacteria while the taste-free Zinc solution naturally freshens the breath & safely cleanses the mouth of dogs & cats. Pet Accapted, Vet Approved.

BENEFITS: Eliminates bad breath, reduces plaque & tartar formations, extends time between dental cleanings.

DIRECTIONS: Wrap wipe around index finger & gently wipe teeth & gums on both sides. More than one wipe may be used if needed. Provide praise to the pet to ensure a positive experience. Use daily for best results.

INGREDIENTS: Deionized Water, Zinc Gluconate, Taurine, Methylparaben, Propylparaben, F.D.& C. Blue #1.

Keep out of reach of children.

DISTRIBUTED BY H&C ANIMAL HEALTH, LLC.

MADE IN THE U.S.A.

Addison Biological Laboratory, Inc.
507 North Cleveland Avenue Fayette, Missouri 65248 USA
www.addisonlabs.com
Rev. 04/20